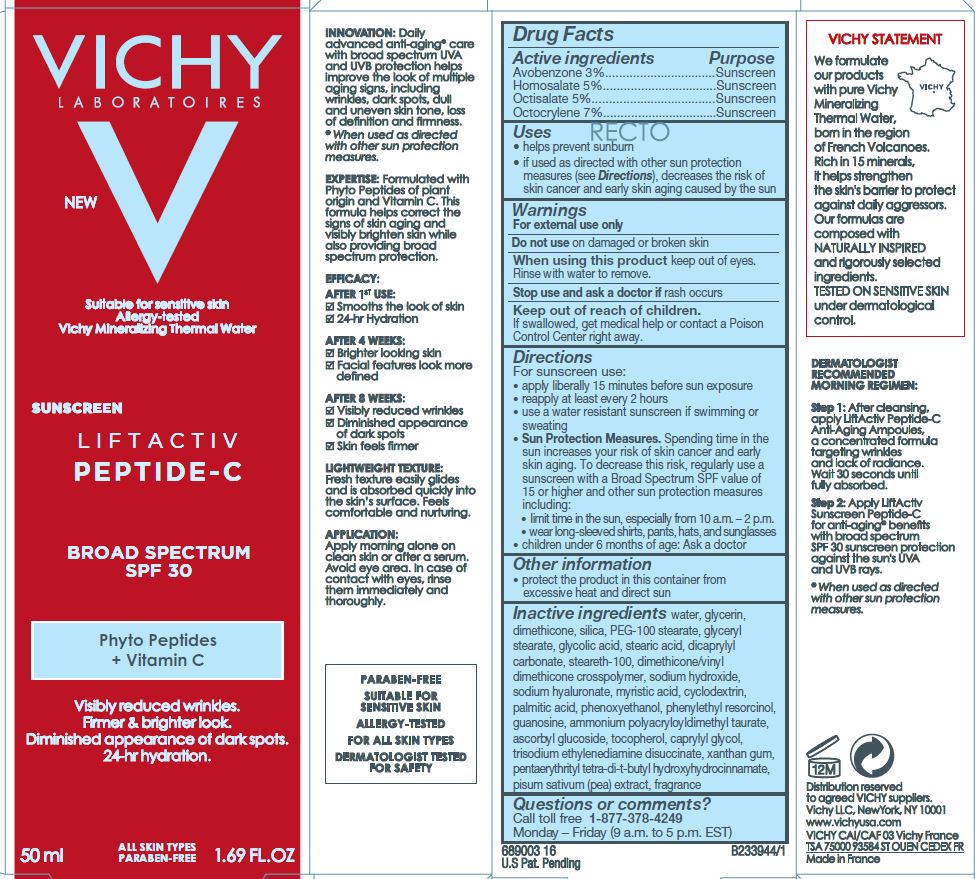 DRUG LABEL: Vichy Laboratories LiftActiv Peptide-C SPF 30 Sunscreen Phyto Peptides Vitamin C
NDC: 69625-685 | Form: LOTION
Manufacturer: Cosmetique Active Products
Category: otc | Type: HUMAN OTC DRUG LABEL
Date: 20231211

ACTIVE INGREDIENTS: AVOBENZONE 30 mg/1 mL; HOMOSALATE 50 mg/1 mL; OCTISALATE 50 mg/1 mL; OCTOCRYLENE 70 mg/1 mL
INACTIVE INGREDIENTS: WATER; GLYCERIN; DIMETHICONE; SILICON DIOXIDE; PEG-100 STEARATE; GLYCERYL MONOSTEARATE; GLYCOLIC ACID; STEARIC ACID; DICAPRYLYL CARBONATE; STEARETH-100; DIMETHICONE/VINYL DIMETHICONE CROSSPOLYMER (SOFT PARTICLE); SODIUM HYDROXIDE; HYALURONATE SODIUM; MYRISTIC ACID; BETADEX; PALMITIC ACID; PHENOXYETHANOL; PHENYLETHYL RESORCINOL; GUANOSINE; AMMONIUM POLYACRYLOYLDIMETHYL TAURATE (55000 MPA.S); ASCORBYL GLUCOSIDE; TOCOPHEROL; caprylyl glycol; TRISODIUM ETHYLENEDIAMINE DISUCCINATE; XANTHAN GUM; PENTAERYTHRITOL TETRAKIS(3-(3,5-DI-TERT-BUTYL-4-HYDROXYPHENYL)PROPIONATE); PEA

Drug Facts

Active ingredients

Avobenzone 3%

Homosalate 5%

Octisalate 5%

Octocrylene 7%

Purpose

Sunscreen

Uses

- help prevent sunburn
- if used as directed with other sun protection measures (see Directions), decreases the risk of skin cancer and early skin aging caused by the sun

Warnings

For external use only

Do not use

on damaged or broken skin

When using this product

keep out of eyes. Rinse with water to remove.

Stop use and ask a doctor if

rash occurs

Keep out of reach of children.

If swallowed, get medical help or contact a Poison Control Center right away.

Directions

For sunscreen use:

- apply liberally 15 minutes before sun exposure
- reapply at least every 2 hours
- use a water resistant sunscreen if swimming or sweating
- Sun Protection Measures. Spending time in the sun increases your risk of skin cancer and early skin aging. To decrease this risk, regularly use a suncreen with a Broad Spectrum SPF value of 15 or higher and other sun protection measures including:
- limit time in the sun, especially from 10 a.m.-2 p.m.
- wear long-sleeved shirts, pants, hats, and sunglasses
- children under 6 months of age: Ask a doctor

Other information

- protect the product in this container from excessive heat and direct sun

Inactive ingredients

water, glycerin, dimethicone, silica, PEG-100 stearate, glyceryl stearate, glycolic acid, stearic acid, dicaprylyl carbonate, steareth-100, dimethicone/vinyl dimethicone crosspolymer, sodium hydroxide, sodium hyaluronate, myristic acid, cyclodextrin, palmitic acid, phenoxyethanol, henylethyl resorcinol, guanosine, ammonium polyacryloyldimethyl taurate, ascorbyl glucoside, tocopherol, caprylyl glycol, trisodium ethylenediamine disuccinate, xanthan gum, pentaerythrityl tetra-di-t-butyl hydroxyhydrocinnamate, pisum sativum (pea) extract, fragrance

Questions or comments?

Call toll free 1-877-378-4249
Monday – Friday (9 a.m. to 5 p.m. EST)